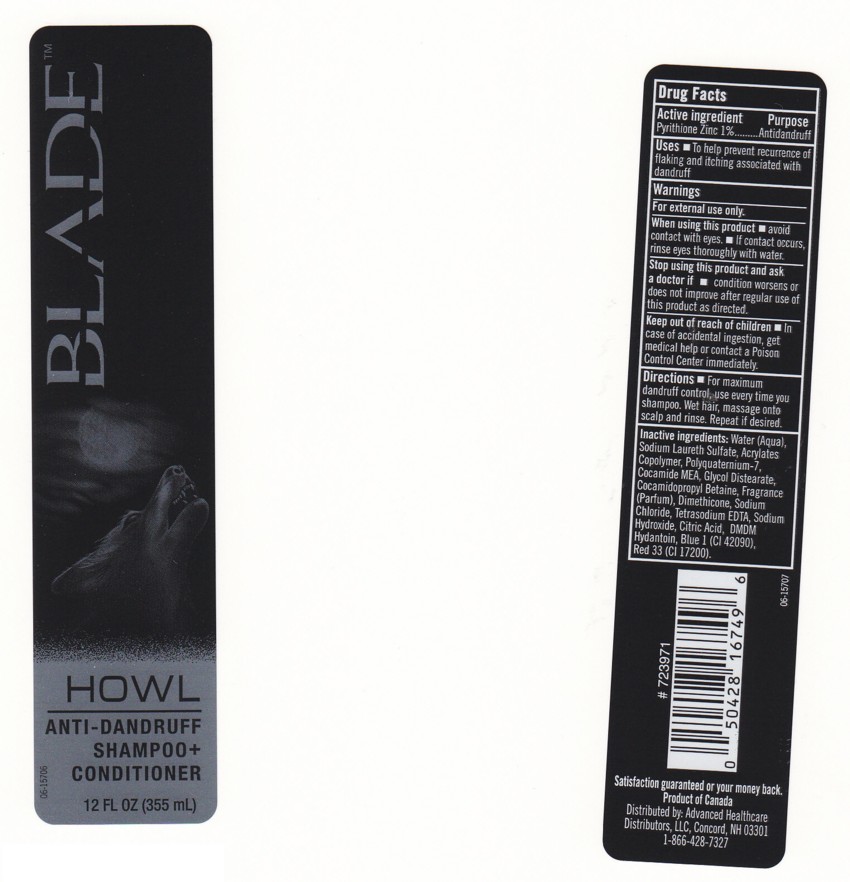 DRUG LABEL: ANTI-DANDRUFF SHAMPOO AND CONDITIONER
NDC: 63148-422 | Form: LOTION/SHAMPOO
Manufacturer: Apollo Health and Beauty Care
Category: otc | Type: HUMAN OTC DRUG LABEL
Date: 20100308

ACTIVE INGREDIENTS: PYRITHIONE ZINC 1.0000 mL/100 mL

Anti-dandruff Shampoo and Conditioner

ACTIVE INGREDIENT

Pyrithione Zinc 1% ............. (Antidandruff)

USES

To help prevent recurrence of flaking and itching associated with dandruff

WARNINGS

For external use only

STOP USING THIS PRODUCT AND ASK A DOCTOR IF

- Condition worsens or does not improve after regular use of this product as directed

WHEN USING THIS PRODUCT

- Avoid contact with eyes
- If contact occurs, rinse eyes throughly with water

KEEP OUT OF REACH OF CHILDREN

- In case of accidental ingestion, get medical help or contact a Poison Control Center immediately

PACKAGE FRONT AND BACK LABELS

- 12 OZ FRONT AND BACK LABELS: blade12.jpg